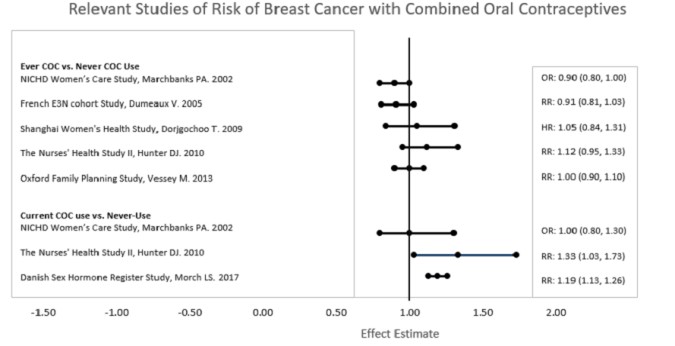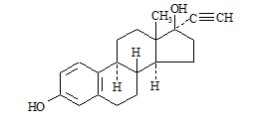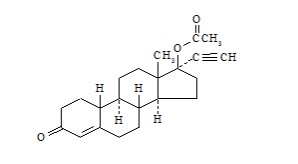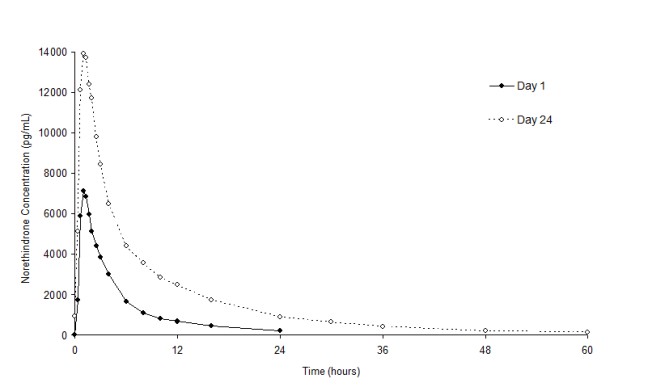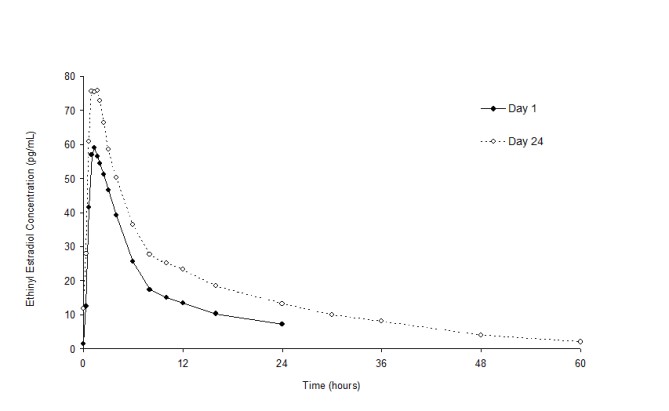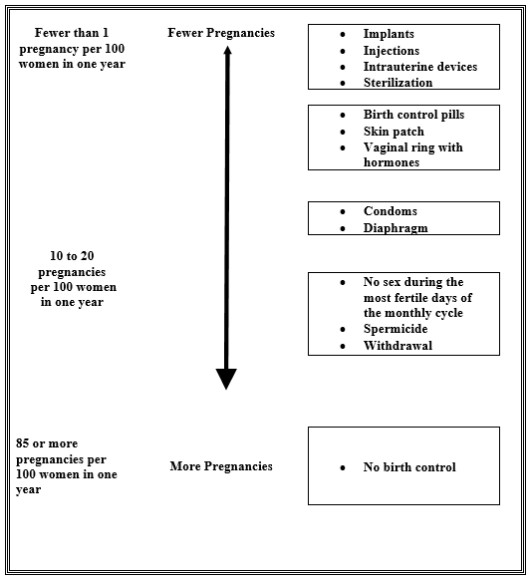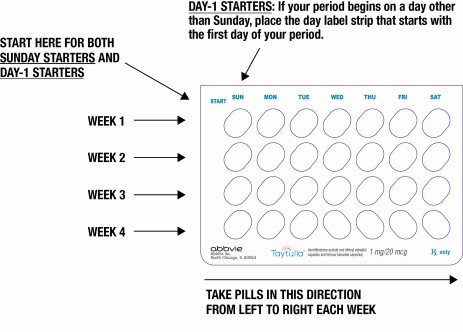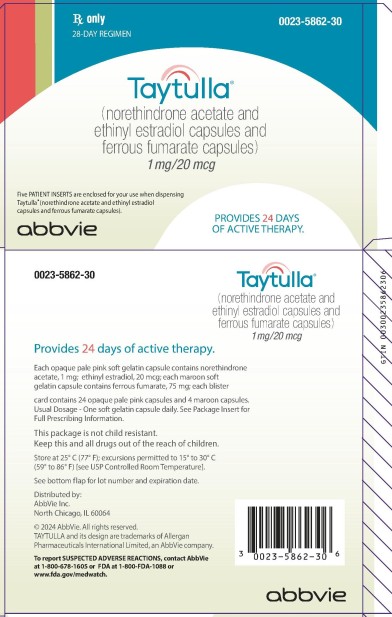 DRUG LABEL: Taytulla
NDC: 0023-5862 | Form: KIT | Route: ORAL
Manufacturer: Allergan, Inc.
Category: prescription | Type: HUMAN PRESCRIPTION DRUG LABEL
Date: 20241025

ACTIVE INGREDIENTS: NORETHINDRONE ACETATE 1 mg/1 1; ETHINYL ESTRADIOL 0.02 mg/1 1
INACTIVE INGREDIENTS: SESAME OIL; PEG-7 LINOLEOYL GLYCERIDES; .ALPHA.-TOCOPHEROL; ALCOHOL; GELATIN; SORBITOL; GLYCERIN; FD&C RED NO. 40; TITANIUM DIOXIDE; FERROUS FUMARATE; SOYBEAN OIL; LECITHIN, SOYBEAN; YELLOW WAX; GELATIN; SORBITOL; GLYCERIN; TITANIUM DIOXIDE; FD&C BLUE NO. 1; FD&C RED NO. 40

HIGHLIGHTS OF PRESCRIBING INFORMATION

These highlights do not include all the information needed to use TAYTULLA® safely and effectively. See full prescribing information for TAYTULLA.
TAYTULLA (norethindrone acetate and ethinyl estradiol capsules and ferrous fumarate capsules), for oral use
Initial U.S. Approval: 1968

WARNING: CIGARETTE SMOKING AND SERIOUS CARDIOVASCULAR EVENTS

See Full Prescribing Information for complete boxed warning.

- Women over 35 years old who smoke should not use TAYTULLA. (4)
- Cigarette smoking increases the risk of serious cardiovascular events from combination oral contraceptive (COC) use. (4)

1 INDICATIONS AND USAGE

- TAYTULLA is a combination of norethindrone acetate, a progestin, and ethinyl estradiol, an estrogen, indicated for use by females of reproductive potential to prevent pregnancy (1)
- The efficacy of TAYTULLA in females of reproductive potential with a body mass index (BMI) of > 35 kg/m^2 has not been evaluated (1, 8.8)

2 DOSAGE AND ADMINISTRATION

- Take one capsule by mouth at the same time every day (2.1)
- Take capsules in the order directed on the blister pack (2.1)
- Capsules may be administered without regard to meals (2.1)

3 DOSAGE FORMS AND STRENGTHS

TAYTULLA consists of 28 soft gelatin capsules in the following order (3):

- 24 pink capsules (active), each containing 1 mg norethindrone acetate and 20 mcg ethinyl estradiol
- 4 maroon capsules (non-hormonal placebo) each containing 75 mg ferrous fumarate which does not serve any therapeutic purpose

4 CONTRAINDICATIONS

- A high risk of arterial or venous thrombotic diseases (4)
- Liver tumors or liver disease (4)
- Undiagnosed abnormal uterine bleeding (4)
- Breast cancer (4)
- Co-administration with Hepatitis C drug combinations containing ombitasvir/paritaprevir/ritonavir, with or without dasabuvir (4)

5 WARNINGS AND PRECAUTIONS

- Vascular risks: Stop TAYTULLA if a thrombotic event occurs. Stop at least 4 weeks before through 2 weeks after major surgery. Start no earlier than 4 weeks after delivery, in women who are not breastfeeding (5.1)
- Liver disease: Discontinue if jaundice occurs (5.2)
- High blood pressure: Do not prescribe TAYTULLA for women with uncontrolled hypertension or hypertension with vascular disease (5.4)
- Carbohydrate and lipid metabolic effects: Monitor prediabetic and diabetic women taking TAYTULLA. Consider an alternative contraceptive method for women with uncontrolled dyslipidemia (5.6)
- Headache: Evaluate significant change in headaches and discontinue TAYTULLA if indicated (5.7)
- Uterine bleeding: Evaluate irregular bleeding or amenorrhea (5.8)

6 ADVERSE REACTIONS

The most common adverse reactions in clinical trials (≥ 2%) are headache, vaginal candidiasis, nausea, menstrual cramps, breast tenderness, bacterial vaginitis, abnormal cervical smear, acne, mood swings, and weight gain (6.1)

To report SUSPECTED ADVERSE REACTIONS, contact AbbVie at 1-800-678-1605 or FDA at 1-800-FDA-1088 or www.fda.gov/medwatch.

7 DRUG INTERACTIONS

- Drugs or herbal products that induce certain enzymes, including CYP3A4, may decrease the effectiveness of COCs or increase breakthrough bleeding. Counsel patients to use a back-up method or alternative method of contraception when enzyme inducers are used with COCs (7.1)

8 USE IN SPECIFIC POPULATIONS

- Lactation: Not recommended; TAYTULLA can decrease milk production (8.2)

FULL PRESCRIBING INFORMATION

WARNING: CIGARETTE SMOKING AND SERIOUS CARDIOVASCULAR EVENTS

Cigarette smoking increases the risk of serious cardiovascular events from combination oral contraceptive (COC) use. This risk increases with age, particularly in women over 35 years of age, and with the number of cigarettes smoked. For this reason, COCs should not be used by women who are over 35 years of age and smoke [see Contraindications (4) and Warnings & Precautions (5.1)].

1 INDICATIONS AND USAGE

TAYTULLA is indicated for use by females of reproductive age to prevent pregnancy [see Clinical Studies (14)].

The efficacy of TAYTULLA in women with a body mass index (BMI) of more than 35 kg/m^2 has not been evaluated.

2 DOSAGE AND ADMINISTRATION

2.1 How to Take TAYTULLA

To achieve maximum contraceptive effectiveness, TAYTULLA must be taken exactly as directed. Instruct patients to take one capsule by mouth at the same time every day. Capsules must be taken in the order directed on the blister pack. Capsules should not be skipped or taken at intervals exceeding 24 hours. TAYTULLA may be administered without regard to meals [see Clinical Pharmacology (12.3)].

2.2 How to Start TAYTULLA

Instruct the patient to begin taking TAYTULLA either on the first day of her menstrual period (Day 1 Start) or on the first Sunday after the onset of her menstrual period (Sunday Start).

Day 1 Start

During the first cycle of TAYTULLA use, instruct the patient to take one pink capsule daily, beginning on Day one (1) of her menstrual cycle (the first day of menstruation is Day one). She should take one pink capsule daily for 24 consecutive days, followed by one maroon capsule daily on days 25 through 28. TAYTULLA should be taken in the order directed on the package at the same time each day. Instruct the patient to use a non-hormonal contraceptive as back-up during the first 7 days if she starts taking TAYTULLA on a day other than the first day of her menstrual cycle. The possibility of ovulation and conception prior to initiation of medication should be considered.

Sunday Start

During the first cycle of TAYTULLA use, instruct the patient to take one pink capsule daily, beginning on the first Sunday after the onset of her menstrual period. She should take one pink capsule daily for 24 consecutive days, followed by one maroon capsule daily on days 25 through 28. TAYTULLA should be taken in the order directed on the package at the same time each day. TAYTULLA should not be considered effective as a contraceptive until after the first 7 consecutive days of product administration. Instruct the patient to use a non-hormonal contraceptive as back-up during the first 7 days. The possibility of ovulation and conception prior to initiation of medication should be considered.

The patient should begin her next and all subsequent 28-day regimens of TAYTULLA on the same day of the week that she began her first regimen, following the same schedule. She should begin taking her pink capsules on the next day after ingestion of the last maroon capsule, regardless of whether or not a menstrual period has occurred or is still in progress. Anytime a subsequent cycle of TAYTULLA is started later than the day following administration of the last maroon capsule, the patient should use another method of contraception until she has taken a pink capsule daily for 7 consecutive days.

For postpartum women who do not breastfeed or after a second trimester abortion, start TAYTULLA no earlier than 4 weeks postpartum due to the increased risk of thromboembolism. If the patient starts TAYTULLA postpartum and has not yet had a period, evaluate for possible pregnancy, and instruct her to use an additional method of contraception until she has taken TAYTULLA for 7 consecutive days.

TAYTULLA may be initiated immediately after a first-trimester abortion or miscarriage; if the patient starts TAYTULLA immediately, additional contraceptive measures are not needed.

Switching from another Hormonal Method of Contraception

If the patient is switching from a combination hormonal method such as:
• Another pill
• Vaginal ring
• Patch

- Instruct her to take the first pink capsule on the day she would have taken her next COC pill. She should not continue taking the tablet from her previous birth control pack and should not skip any days between packs. If she does not have a withdrawal bleed, rule out pregnancy before starting TAYTULLA.
- If she previously used a vaginal ring or transdermal patch, she should start using TAYTULLA on the day she would have resumed the previous product.

If the patient is switching from a progestin-only method such as a:
• Progestin-only pill
• Implant
• Intrauterine system
• Injection

- She may switch any day from a progestin-only pill; instruct her to take the first pink capsule on the day she would have taken her next progestin-only pill. She should use a non-hormonal method of contraception for 7 consecutive days.
- If switching from an implant or injection, start the first pink capsule on the day her next injection would have been due or on the day of removal of her implant.
- If switching from an IUD, depending on the timing of removal, back-up contraception may be needed.

2.3 Missed Doses

Table 1. Instructions for Missed TAYTULLA Capsules
If one pink capsule is missed | Take the missed capsule as soon as possible. Take the next capsule at the regular time. Continue taking one capsule a day until the pack is finished. Additional nonhormonal contraception (such as condoms) is not needed.
If two pink capsules in a row are missed in Week 1 or Week 2 of the capsule pack | Take the two missed capsules as soon as possible, and the next two capsules the next day. Continue taking one capsule a day until the pack is finished. Use additional nonhormonal contraception (such as condoms) until hormonal capsules have been taken for 7 days after missing capsules.
If two pink capsules in a row are missed in Week 3 or Week 4 of the capsule pack | Day 1 Starter: Throw out the rest of the TAYTULLA pack and start a new pack that same day. Sunday Starter: Keep taking one capsule every day until Sunday. On Sunday, throw out the rest of the pack and start a new pack of capsules that same day. Use additional nonhormonal contraception (such as condoms) until hormonal capsules have been taken for 7 days after missing capsules.
If three or more pink capsules in a row are missed | Day 1 Starter: Throw out the rest of the TAYTULLA pack and start a new pack that same day. Sunday Starter: Keep taking one capsule every day until Sunday. On Sunday, throw out the rest of the pack and start a new pack of capsules that same day. Bleeding may occur during the week following the missed capsules. Use additional nonhormonal contraception (such as condoms) until hormonal capsules have been taken for 7 days after missing capsules.
If any of the four maroon capsules are missed | Throw away the missed capsules. Continue taking the remaining capsules until the pack is finished. Additional nonhormonal contraception (such as condoms) is not needed.

2.4 Advice in Case of Gastrointestinal Disturbances

If the patient vomits or has diarrhea (within 3 to 4 hours after she takes a pink capsule), she should follow the instructions in the “What to Do if You Miss Capsules” section [see Dosage and Administration (2.3)].

3 DOSAGE FORMS AND STRENGTHS

TAYTULLA is available in blister packs.

Each blister pack contains 28 soft gelatin capsules in the following order:

- 24 oval, opaque, pale pink (active) soft gelatin capsule with “WC” printed on the outer shell in white and each containing 1 mg norethindrone acetate and 20 mcg ethinyl estradiol.
- 4 oval, opaque, maroon, (non-hormonal placebo) capsules imprinted with “WC” on one side and each containing 75 mg ferrous fumarate. The ferrous fumarate capsules do not serve any therapeutic purpose.

4 CONTRAINDICATIONS

TAYTULLA is contraindicated in females who are known to have or develop the following conditions:

- A high risk of arterial or venous thrombotic diseases. Examples include women who are known to:
  • Smoke, if over age 35 [see Boxed Warning and Warnings and Precautions (5.1)]
  • Have deep vein thrombosis or pulmonary embolism, now or in the past [see Warnings and Precautions (5.1)]
  • Have cerebrovascular disease [see Warnings and Precautions (5.1)]
  • Have coronary artery disease [see Warnings and Precautions (5.1)]
  • Have thrombogenic valvular or thrombogenic rhythm diseases of the heart (for example, subacute bacterial endocarditis with valvular disease, or atrial fibrillation) [see Warnings and Precautions (5.1)]
  • Have inherited or acquired hypercoagulopathies [see Warnings and Precautions (5.1)]
  • Have uncontrolled hypertension [see Warnings and Precautions (5.4)]
  • Have diabetes mellitus with vascular disease [see Warnings and Precautions (5.6)]
  • Have headaches with focal neurological symptoms or have migraine headaches with aura
  • Women over age 35 with any migraine headaches [see Warnings and Precautions (5.7)]
- Liver tumors, benign or malignant, or liver disease [see Warnings and Precautions (5.2)]
- Undiagnosed abnormal uterine bleeding [see Warnings and Precautions (5.8)]
- Current diagnosis of, or history of, breast cancer, which may be hormone-sensitive [see Warnings and Precautions (5.11)]
- Use of Hepatitis C drug combinations containing ombitasvir/paritaprevir/ritonavir, with or without dasabuvir, due to the potential for ALT elevations [see Warnings and Precautions (5.3)]

5 WARNINGS AND PRECAUTIONS

5.1 Thromboembolic Disorders and Other Vascular Problems

Stop TAYTULLA if an arterial or deep venous thrombotic event (VTE) occurs. Stop TAYTULLA if there is unexplained loss of vision, proptosis, diplopia, papilledema, or retinal vascular lesions. Evaluate for retinal vein thrombosis immediately.

If feasible, stop TAYTULLA at least 4 weeks before and through 2 weeks after major surgery or other surgeries known to have an elevated risk of VTE.

Start TAYTULLA no earlier than 4 weeks after delivery, in women who are not breastfeeding. The risk of postpartum VTE decreases after the third postpartum week, whereas the risk of ovulation increases after the third postpartum week.

The use of COCs increases the risk of VTE. However, pregnancy increases the risk of VTE as much or more than the use of COCs. The risk of VTE in women using COCs is 3 to 9 per 10,000 woman-years. The risk of VTE is highest during the first year of use of a COC. The risk of thromboembolic disease due to oral contraceptives gradually disappears after COC use is discontinued.

Use of COCs also increases the risk of arterial thromboses such as strokes and myocardial infarctions, especially in women with other risk factors for these events. COCs have been shown to increase both the relative and attributable risks of cerebrovascular events (thrombotic and hemorrhagic strokes), although, in general, the risk is greatest in older (> 35 years of age), hypertensive women who also smoke. COCs also increase the risk for stroke in women with underlying risk factors.

Use COCs with caution in women with cardiovascular disease risk factors.

5.2 Liver Disease

Impaired Liver Function

Do not use TAYTULLA in women with acute viral hepatitis or severe (decompensated) cirrhosis of liver [see Contraindications (4)]. Acute or chronic disturbances of liver function may necessitate the discontinuation of COC use until markers of liver function return to normal and COC causation has been excluded. Discontinue TAYTULLA if jaundice develops.

Liver Tumors

TAYTULLA is contraindicated in women with benign and malignant liver tumors [see Contraindications (4)]. Hepatic adenomas are associated with COC use. An estimate of the attributable risk is 3.3 cases per 100,000 COC users. Rupture of hepatic adenomas may cause death through intra-abdominal hemorrhage.

Studies have shown an increased risk of developing hepatocellular carcinoma in long-term (>8 years) COC users. However, the attributable risk of liver cancers in COC users is less than one case per million users.

5.3 Risk of Liver Enzyme Elevations with Concomitant Hepatitis C Treatment

During clinical trials with the Hepatitis C combination drug regimen that contains ombitasvir/ paritaprevir / ritonavir, with or without dasabuvir, ALT elevations greater than 5 times the upper limit of normal (ULN), including some cases greater than 20 times the ULN, were significantly more frequent in women using ethinyl estradiol-containing medications, such as COCs. Discontinue TAYTULLA prior to starting therapy with the combination drug regimen ombitasvir/paritaprevir/ritonavir, with or without dasabuvir [see Contraindications (4)]. TAYTULLA can be restarted approximately 2 weeks following completion of treatment with the Hepatitis C combination drug regimen.

5.4 High Blood Pressure

TAYTULLA is contraindicated in women with uncontrolled hypertension or hypertension with vascular disease [see Contraindications (4)]. For women with well-controlled hypertension, monitor blood pressure and stop TAYTULLA if blood pressure rises significantly.

An increase in blood pressure has been reported in women taking COCs, and this increase is more likely in older women with extended duration of use. The incidence of hypertension increases with increasing concentrations of progestin.

5.5 Gallbladder Disease

Studies suggest a small increased relative risk of developing gallbladder disease among COC users. Use of COCs may also worsen existing gallbladder disease.

A past history of COC-related cholestasis predicts an increased risk with subsequent COC use. Women with a history of pregnancy-related cholestasis may be at an increased risk for COC-related cholestasis.

5.6 Carbohydrate and Lipid Metabolic Effects

Carefully monitor prediabetic and diabetic women who are taking TAYTULLA. COCs may decrease glucose tolerance in a dose-related fashion.

Consider alternative contraception for women with uncontrolled dyslipidemias. A small proportion of women will have adverse lipid changes while on COCs.

Women with hypertriglyceridemia, or a family history thereof, may be at an increased risk of pancreatitis when using COCs.

5.7 Headache

If a woman taking TAYTULLA develops new headaches that are recurrent, persistent, or severe, evaluate the cause and discontinue TAYTULLA if indicated.

Consider discontinuation of TAYTULLA in the case of increased frequency or severity of migraine during COC use (which may be prodromal of a cerebrovascular event) [see Contraindications (4)].

5.8 Bleeding Irregularities and Amenorrhea

Unscheduled Bleeding and Spotting

Unscheduled (breakthrough or intracyclic) bleeding and spotting sometimes occur in patients on COCs, especially during the first three months of use. If bleeding persists or occurs after previously regular cycles, check for causes such as pregnancy or malignancy. If pathology and pregnancy are excluded, bleeding irregularities may resolve over time or with a change to a different COC.

Based on patient diaries from a clinical trial evaluating the safety and efficacy of a 24-day regimen of norethindrone acetate 1 mg/ethinyl estradiol 0.020 mg tablets, 24-35% of women experienced unscheduled bleeding per cycle. A total of 10 subjects out of 743 (1.3%) discontinued due to bleeding or spotting.

Amenorrhea and Oligomenorrhea

Women who are not pregnant and use TAYTULLA may experience amenorrhea. In the clinical trial with a 24-day regimen of norethindrone acetate 1 mg/ethinyl estradiol 0.020 mg tablets, 22 to 36% of the women using norethindrone acetate 1 mg/ethinyl estradiol 0.020 mg tablets experienced amenorrhea in at least one of 6 cycles of use. Some women may experience post-pill amenorrhea or oligomenorrhea, especially when such a condition was preexistent.

If scheduled (withdrawal) bleeding does not occur, consider the possibility of pregnancy. If the patient has not adhered to the prescribed dosing schedule (missed one or more active capsules or started taking them on a day later than she should have), consider the possibility of pregnancy at the time of the first missed period and take appropriate diagnostic measures. If the patient has adhered to the prescribed regimen and misses two consecutive periods, rule out pregnancy.

5.9 COC Use before or during Early Pregnancy

Extensive epidemiologic studies have revealed no increased risk of birth defects in women who have used oral contraceptives prior to pregnancy. Studies also do not suggest a teratogenic effect, particularly in so far as cardiac anomalies and limb reduction defects are concerned when oral contraceptives are taken inadvertently during early pregnancy. Discontinue TAYTULLA if pregnancy is confirmed.

Administration of oral contraceptives to induce withdrawal bleeding should not be used as a test for pregnancy [see Use in Specific Populations (8.1)].

5.10 Depression

Carefully observe women with a history of depression and discontinue TAYTULLA if depression recurs to a serious degree.

5.11 Malignant Neoplasms

Breast Cancer

TAYTULLA is contraindicated in females who currently have or have had breast cancer because breast cancer may be hormonally sensitive [see Contraindications (4)].

Epidemiology studies have not found a consistent association between use of combined oral contraceptives (COCs) and breast cancer risk. Studies do not show an association between ever (current or past) use of COCs and risk of breast cancer. However, some studies report a small increase in the risk of breast cancer among current or recent users (<6 months since last use) and current users with longer duration of COC use [see Adverse Reactions (6.2)].

Cervical Cancer

Some studies suggest that COCs are associated with an increase in the risk of cervical cancer or intraepithelial neoplasia. However, there is controversy about the extent to which these findings may be due to differences in sexual behavior and other factors.

5.12 Effect on Binding Globulins

The estrogen component of COCs may raise the serum concentrations of thyroxine-binding globulin, sex hormone-binding globulin and cortisol-binding globulin. The dose of replacement thyroid hormone or cortisol therapy may need to be increased.

5.13 Monitoring

A woman who is taking COCs should have a yearly visit with her healthcare provider for a blood pressure check and for other indicated healthcare.

5.14 Hereditary Angioedema

In women with hereditary angioedema, exogenous estrogens may induce or exacerbate symptoms of angioedema.

5.15 Chloasma

Chloasma may occasionally occur, especially in women with a history of chloasma gravidarum. Women with a tendency to chloasma should avoid exposure to the sun or ultraviolet radiation while taking TAYTULLA.

6 ADVERSE REACTIONS

The following serious adverse reactions with the use of COCs are discussed elsewhere in the labeling:

- Serious cardiovascular events and stroke [see Boxed Warning and Warnings and Precautions (5.1)]
- Vascular events [see Warnings and Precautions (5.1)]
- Liver disease [see Warnings and Precautions (5.2)]

Adverse reactions commonly reported by COC users are:

- Irregular uterine bleeding
- Nausea
- Breast tenderness
- Headache

6.1 Clinical Trial Experience

Because clinical trials are conducted under widely varying conditions, adverse reaction rates observed in the clinical trials of a drug cannot be directly compared to the rates in the clinical trials of another drug and may not reflect the rates observed in practice. The data presented in Section 6.1 are from a clinical trial conducted with a 24-day regimen of norethindrone acetate 1 mg/ethinyl estradiol 0.020 mg tablets. TAYTULLA capsules are bioequivalent to these norethindrone acetate/ethinyl estradiol tablets.

Common Adverse Reactions (≥ 2% of all Treated Subjects): The most common adverse reactions reported by at least 2% of the 743 women using norethindrone acetate/ethinyl estradiol tablets were the following, in order of decreasing incidence: headache (6.3%), vaginal candidiasis (6.1%), nausea (4.6%), menstrual cramps (4.4%), breast tenderness (3.4%), bacterial vaginitis (3.1%), abnormal cervical smear (3.1%), acne (2.7%), mood swings (2.2%), and weight gain (2.0%).

Adverse Reactions Leading to Study Discontinuation: Among the 743 women using norethindrone acetate/ethinyl estradiol tablets, 46 women (6.2%) withdrew because of an adverse event. Adverse events occurring in 3 or more subjects leading to discontinuation of treatment were, in decreasing order: abnormal or irregular bleeding (1.3%), nausea (0.8%), menstrual cramps (0.5%), and increased blood pressure (0.4%).

6.2 Postmarketing Experience

Five studies that compared breast cancer risk between ever-users (current or past use) of COCs and never-users of COCs reported no association between ever use of COCs and breast cancer risk, with effect estimates ranging from 0.90 - 1.12 (Figure 1).

Three studies compared breast cancer risk between current or recent COC users (<6 months since last use) and never users of COCs (Figure 1). One of these studies reported no association between breast cancer risk and COC use. The other two studies found an increased relative risk of 1.19 - 1.33 with current or recent use. Both of these studies found an increased risk of breast cancer with current use of longer duration, with relative risks ranging from 1.03 with less than one year of COC use to approximately 1.4 with more than 8-10 years of COC use.

Figure 1.

RR = relative risk; OR = odds ratio; HR = hazard ratio. “ever COC” are females with current or past COC use; “never COC use” are females that never used COCs.

The following adverse reactions have been identified during post approval use of a 24-day regimen of norethindrone acetate 1 mg/ethinyl estradiol 0.020 mg tablets. Because these reactions are reported voluntarily from a population of uncertain size, it is not always possible to reliably estimate their frequency or evaluate a causal relationship to drug exposure.

Vascular disorders: thrombosis/embolism (coronary artery, pulmonary, cerebral, deep vein).

Hepatobiliary disorders: cholelithiasis, cholecystitis, hepatic adenoma, hemangioma of liver.

Immune system disorders: hypersensitivity reaction.

Skin and subcutaneous disorders: alopecia, rash (generalized and allergic), pruritus, skin discoloration.

GI disorders: nausea, vomiting, abdominal pain.

Musculoskeletal and connective tissue disorders: myalgia.

Eye disorders: blurred vision, visual impairment, corneal thinning, change in corneal curvature (steepening).

Infections and infestations: fungal infection, vaginal infection.

Investigations: change in weight or appetite (increase or decrease), fatigue, malaise, peripheral edema, blood pressure increased.

Nervous system disorders: headache, dizziness, migraine, loss of consciousness.

Psychiatric disorders: mood swings, depression, insomnia, anxiety, suicidal ideation, panic attack, changes in libido.

Renal and urinary disorders: cystitis-like syndrome.

Reproductive system and breast disorders: breast changes (tenderness, pain, enlargement, and secretion), premenstrual syndrome, dysmenorrhea.

Cardiovascular: chest pain, palpitations, tachycardia, myocardial infarction.

7 DRUG INTERACTIONS

Consult the labeling of the concurrently-used drug to obtain further information about interactions with COCs or the potential for enzyme alterations.

7.1 Effects of Other Drugs on Combined Oral Contraceptives

Substances diminishing the efficacy of COCs: Drugs or herbal products that induce certain enzymes, including cytochrome P450 3A4 (CYP3A4), may decrease the effectiveness of COCs or increase breakthrough bleeding. Some drugs or herbal products that may decrease the effectiveness of hormonal contraceptives include phenytoin, barbiturates, carbamazepine, bosentan, felbamate, griseofulvin, oxcarbazepine, rifampicin, topiramate and products containing St. John’s wort. Interactions between oral contraceptives and other drugs may lead to breakthrough bleeding and/or contraceptive failure. Counsel women to use an alternative method of contraception or a back-up method when enzyme inducers are used with COCs, and to continue back-up contraception for 28 days after discontinuing the enzyme inducer to ensure contraceptive reliability.

Substances increasing the plasma concentrations of COCs: Co-administration of atorvastatin and certain COCs containing ethinyl estradiol increase AUC values for ethinyl estradiol by approximately 20%. Ascorbic acid and acetaminophen may increase plasma ethinyl estradiol concentrations, possibly by inhibition of conjugation. CYP3A4 inhibitors such as itraconazole or ketoconazole may increase plasma hormone concentrations.

Human immunodeficiency virus (HIV)/ Hepatitis C virus (HCV) protease inhibitors and non-nucleoside reverse transcriptase inhibitors: Significant changes (increase or decrease) in the plasma concentrations of estrogen and progestin have been noted in some cases of co-administration with HIV/HCV protease inhibitors or with non-nucleoside reverse transcriptase inhibitors.

Antibiotics: There have been reports of pregnancy while taking hormonal contraceptives and antibiotics, but clinical pharmacokinetic studies have not shown consistent effects of antibiotics on plasma concentrations of synthetic steroids.

7.2 Effects of Combined Oral Contraceptives on Other Drugs

COCs containing ethinyl estradiol may inhibit the metabolism of other compounds. COCs have been shown to significantly decrease plasma concentrations of lamotrigine, likely due to induction of lamotrigine glucuronidation. This may reduce seizure control; therefore, dosage adjustments of lamotrigine may be necessary.

Women on thyroid hormone replacement therapy may need increased doses of thyroid hormone because serum concentration of thyroid-binding globulin increases with use of COCs.

7.3 Concomitant Use with HCV Combination Therapy – Liver Enzyme Elevation

Do not co-administer TAYTULLA with HCV drug combinations containing ombitasvir/paritaprevir/ritonavir, with or without dasabuvir, due to potential for ALT elevations [see Warnings and Precautions (5.3)].

7.4 Interference with Laboratory Tests

The use of contraceptive steroids may influence the results of certain laboratory tests, such as coagulation factors, lipids, glucose tolerance, and binding proteins.

8 USE IN SPECIFIC POPULATIONS

8.1 Pregnancy

Risk Summary

There is no use for contraception in pregnancy; therefore, TAYTULLA should be discontinued during pregnancy. Epidemiologic studies and meta-analyses have not found an increased risk of genital or nongenital birth defects (including cardiac anomalies and limb-reduction defects) following exposure to COCs before conception or during early pregnancy.

In the U.S. general population, the estimated background risk of major birth defects and miscarriage in clinically recognized pregnancies is 2 to 4 percent and 15 to 20 percent, respectively.

8.2 Lactation

Risk Summary

Contraceptive hormones and/or metabolites are present in human milk. COCs can reduce milk production in breast-feeding females. This reduction can occur at any time but is less likely to occur once breast-feeding is well-established. When possible, advise the nursing female to use other methods of contraception until she discontinues breast-feeding [see Dosage and Administration (2.2)]. The developmental and health benefits of breast-feeding should be considered along with the mother’s clinical need for TAYTULLA and any potential adverse effects on the breast-fed child from TAYTULLA or from the underlying maternal condition.

8.4 Pediatric Use

Safety and efficacy of TAYTULLA have been established in women of reproductive age. Efficacy is expected to be the same in postpubertal adolescents under the age of 18 years as for users 18 years and older. Use of this product before menarche is not indicated.

8.5 Geriatric Use

TAYTULLA has not been studied in postmenopausal women and is not indicated in this population.

8.6 Renal Impairment

The pharmacokinetics of TAYTULLA has not been studied in subjects with renal impairment [see Clinical Pharmacology (12.3)].

8.7 Hepatic Impairment

The pharmacokinetics of TAYTULLA has not been studied in subjects with hepatic impairment. However, steroid hormones may be poorly metabolized in patients with hepatic impairment. Acute or chronic disturbances of liver function may necessitate the discontinuation of COC use until markers of liver function return to normal and COC causation has been excluded [see Contraindications (4) and Warnings and Precautions (5.2)].

8.8 Body Mass Index

The safety and efficacy of TAYTULLA in women with a body mass index (BMI) >35 kg/m^2 has not been evaluated [see Clinical Studies (14)].

10 OVERDOSAGE

There have been no reports of serious ill effects from overdose of oral contraceptives, including ingestion by children. Overdosage may cause withdrawal bleeding in females and nausea.

11 DESCRIPTION

TAYTULLA (Norethindrone Acetate and Ethinyl Estradiol Capsules and Ferrous Fumarate Capsules) contain norethindrone acetate, a progestin, and ethinyl estradiol, an estrogen. TAYTULLA provides an oral contraceptive regimen consisting of 24 pink active soft gelatin capsules that contain the active ingredients, followed by 4 maroon non-hormonal placebo soft gelatin capsules as specified below:

- 24 oval, opaque, pale pink soft gelatin capsules each containing 1 mg norethindrone acetate and 20 mcg ethinyl estradiol.
- 4 oval, opaque, maroon, capsules each containing 75 mg ferrous fumarate

Each pink active capsule also contains the following inactive ingredients: sesame oil, linoleoyl polyoxylglycerides, DL-α-tocopherol, dehydrated alcohol, gelatin, sorbitol and glycerin, FD&C Red #40, and titanium dioxide.

Each maroon non-hormonal placebo capsule contains ferrous fumarate, soybean oil, lecithin, yellow beeswax, gelatin, sorbitol, glycerin, FD&C Blue #1, FD&C Red #40 and titanium dioxide. The ferrous fumarate capsules do not serve any therapeutic purpose.

The chemical name of ethinyl estradiol is [19-Norpregna-1,3,5(10)-trien-20-yne-3,17-diol, (17α)-]. The empirical formula of ethinyl estradiol is C20H24O2 and the structural formula is:

The chemical name of norethindrone acetate is [19-Norpregn-4-en-20-yn-3-one, 17-(acetyloxy)-, (17α)-]. The empirical formula of norethindrone acetate is C22H28O3 and the structural formula is:

12 CLINICAL PHARMACOLOGY

12.1 Mechanism of Action

CHCs lower the risk of becoming pregnant primarily by suppressing ovulation.

12.2 Pharmacodynamics

No specific pharmacodynamic studies were conducted with TAYTULLA.

12.3 Pharmacokinetics

Absorption

In a single-dose, crossover clinical study conducted in 39 healthy, non-smoking premenopausal women under fasting condition, TAYTULLA capsules were bioequivalent to norethindrone acetate 1 mg/ethinyl estradiol 0.020 mg tablets (24-day regimen tablets) based on the exposure (AUC) and peak concentration (Cmax) of norethindrone and ethinyl estradiol.

Norethindrone acetate appears to be completely and rapidly deacetylated to norethindrone after oral administration, because the disposition of norethindrone acetate is indistinguishable from that of orally administered norethindrone. Norethindrone acetate and ethinyl estradiol are rapidly absorbed from norethindrone acetate/ethinyl estradiol tablets, with maximum plasma concentrations of norethindrone and ethinyl estradiol occurring 1 to 4 hours post-dose. Both are subject to first-pass metabolism after oral dosing, resulting in an absolute bioavailability of approximately 64% for norethindrone and 43% for ethinyl estradiol.

The plasma norethindrone and ethinyl estradiol pharmacokinetics following single- and multiple-dose administrations of norethindrone acetate/ethinyl estradiol tablets in 17 healthy female volunteers are provided in Figures 2 and 3, and Table 2.

Following multiple-dose administration of norethindrone acetate/ethinyl estradiol tablets, mean maximum concentrations of norethindrone and ethinyl estradiol were increased by 95% and 27%, respectively, as compared to single-dose administration. Mean norethindrone and ethinyl estradiol exposures (AUC values) were increased by 164% and 51% respectively, as compared to single-dose administration of norethindrone acetate/ethinyl estradiol tablets.

Steady-state with respect to norethindrone was reached by Day 17 and steady-state with respect to ethinyl estradiol was reached by Day 13.

Mean SHBG concentrations were increased by 150% from baseline (57.5 nmol/L) to 144 nmol/L at steady-state.

Figure 2. Mean Plasma Norethindrone Concentration-Time Profiles Following Single- and Multiple-Dose Oral Administration of Norethindrone Acetate/Ethinyl Estradiol Tablets to Healthy Female Volunteers under Fasting Condition (n = 17)

Figure 3. Mean Plasma Ethinyl Estradiol Concentration-Time Profiles Following Single- and Multiple-Dose Oral Administration of Norethindrone Acetate/Ethinyl Estradiol Tablets to Healthy Female Volunteers Under Fasting Condition (n = 17)

Table 2. Summary of Norethindrone (NE) and Ethinyl Estradiol (EE) Pharmacokinetics Following Single- and Multiple-Dose Oral Administration of Norethindrone Acetate/Ethinyl Estradiol Tablets to Healthy Female Volunteers Under Fasting Condition (n = 17)
Regimen | Analyte | Arithmetic Meana (% CV) by Pharmacokinetic Parameter
 |  | Cmax (pg/mL) | tmax (hr) | AUC(0-24) (pg/mL•h) | Cmin (pg/mL) | t½ (hr) | Cavg (pg/mL)
Day 1 (Single Dose) | NE | 8420 (31) | 1.0 (0.7-4.0) | 33390 (40) | -- | -- | --
 | EE | 64.5 (27) | 1.3 (0.7-4.0) | 465.4 (26) | -- | -- | --
 | SHBG | -- | -- | -- | 57.5 (37)b | -- | --
Day 24 (Multiple Dose) | NE | 16400 (26) | 1.3 (0.7-4.0) | 88160 (30) | 880 (51) | 8.4 | 3670 (30)
 | EE | 81.9 (24) | 1.7 (1.0-2.0) | 701.3 (28) | 11.4 (43) | 14.5 | 29.2 (28)
 | SHBG | -- | -- | -- | 144 (24) | -- | --
Cmax = Maximum plasma concentration
tmax = Time of Cmax
Cmin = minimum plasma concentration at steady-state
AUC(0-24) = Area under plasma concentration versus time curve from 0 to 24 hours
t½ = Apparent first-order terminal elimination half-life
Cavg = Average plasma concentration = AUC(0–24)/24
% CV = Coefficient of Variation (%)
SHBG = Sex Hormone Binding Globulin (nmol/L)
aThe harmonic mean (0.693/mean apparent elimination rate constant) is reported for t½, and the median (range) is reported for tmax.
bThe SHBG concentration reported here is the pre-dose concentration.

Food Effect

TAYTULLA may be administered without regard to meals.

A single-dose administration of TAYTULLA capsules with food in 38 healthy, non-smoking premenopausal women decreased the maximum concentration of norethindrone and ethinyl estradiol by 38% and 33%, respectively. Food intake did not affect the extent of ethinyl estradiol absorption, but increased the extent of norethindrone absorption by 19%.

Distribution

Volume of distribution of norethindrone and ethinyl estradiol ranges from 2 to 4 L/kg. Plasma protein binding of both steroids is extensive (>95%); norethindrone binds to both albumin and SHBG, whereas ethinyl estradiol binds only to albumin. Although ethinyl estradiol does not bind to SHBG, it induces SHBG synthesis.

Metabolism

Norethindrone undergoes extensive biotransformation, primarily via reduction, followed by sulfate and glucuronide conjugation. The majority of metabolites in the circulation are sulfates, with glucuronides accounting for most of the urinary metabolites.

Ethinyl estradiol is also extensively metabolized, both by oxidation and by conjugation with sulfate and glucuronide. Sulfates are the major circulating conjugates of ethinyl estradiol and glucuronides predominate in urine. The primary oxidative metabolite is 2-hydroxy ethinyl estradiol, formed by the CYP3A4 isoform of cytochrome P450. Part of the first-pass metabolism of ethinyl estradiol is believed to occur in gastrointestinal mucosa. Ethinyl estradiol may undergo enterohepatic circulation.

Excretion

Norethindrone and ethinyl estradiol are excreted in both urine and feces, primarily as metabolites. Plasma clearance values for norethindrone and ethinyl estradiol are similar (approximately 0.4 L/hr/kg). Steady-state elimination half-lives of norethindrone and ethinyl estradiol following administration of norethindrone acetate/ethinyl estradiol tablets are approximately 8 hours and 14 hours, respectively.

Drug Interactions

No drug-drug interaction studies were conducted with TAYTULLA.

13 NONCLINICAL TOXICOLOGY

13.1 Carcinogenesis, Mutagenesis, Impairment of Fertility

[See Warnings and Precautions (5.2, 5.11)]

14 CLINICAL STUDIES

The data presented in Section 14 are from a clinical trial conducted with a 24-day regimen of norethindrone acetate 1 mg/ethinyl estradiol 0.020 mg tablets. TAYTULLA capsules are bioequivalent to these norethindrone acetate/ethinyl estradiol tablets.

In a clinical study, 743 women 18 to 45 years of age were studied to assess the efficacy of norethindrone acetate/ethinyl estradiol tablets, for up to six 28-day cycles providing a total of 3,823 treatment-cycles of exposure. The racial demographic of all enrolled women was: 70% Caucasian, 16% African-American, 10% Hispanic, 2% Asian and 2% Other. Women with body mass index (BMI) greater than 35 mg/m^2 were excluded from the study. The weight range for those women treated was 90 to 260 pounds, with a mean weight of 147 pounds. Among the women in the study, about 40% had not used hormonal contraception immediately prior to enrolling in this study.

A total of 583 women completed 6 cycles of treatment. There were a total of 5 on-treatment pregnancies in 3,565 treatment cycles during which no backup contraception was used. The Pearl Index for norethindrone acetate/ethinyl estradiol tablets was 1.82 (95% confidence interval 0.59 - 4.25).

16 HOW SUPPLIED/STORAGE AND HANDLING

16.1 How Supplied

TAYTULLA (norethindrone acetate and ethinyl estradiol capsules and ferrous fumarate capsules) is available in blister cards (dispensers) containing 28 soft gelatin capsules:

Each blister card contains 28 capsules in the following order:

- 24 oval, opaque, pale pink (active) soft gelatin capsule with “WC” printed on the outer shell in white and each containing 1 mg norethindrone acetate and 20 mcg ethinyl estradiol.
- 4 oval, opaque, maroon, (non-hormonal placebo) capsules imprinted with “WC” on one side and each containing 75 mg ferrous fumarate. The ferrous fumarate capsules do not serve any therapeutic purpose.

Each blister card is packed in a carton (NDC 0023-5862-28).

Cartons of 5 blister cards packed individually in 5 cartons are provided for dispensing (NDC 0023-5862-30). 5 cartons - each carton contains 1 blister card (28): NDC 0023-5862-28

16.2 Storage Conditions

Store at 25º C (77º F); excursions permitted to 15 to 30º C (59 to 86º F) [see USP Controlled Room Temperature].

17 PATIENT COUNSELING INFORMATION

See FDA-approved patient labeling (Patient Information).

Counsel patients on the following information:

- Cigarette smoking increases the risk of serious cardiovascular events from COC use, and women who are over 35 years old and smoke should not use COCs.
- Increased risk of VTE compared to non-users of COCs is greatest after initially starting a COC or restarting (following a 4-week or greater pill-free interval) the same or a different COC.
- TAYTULLA does not protect against HIV infection (AIDS) and other sexually transmitted infections.
- The Warnings and Precautions associated with COCs.
- TAYTULLA is not to be used during pregnancy; if pregnancy occurs during use of TAYTULLA, instruct the patient to stop further intake.
- Take one capsule daily by mouth at the same time every day. Instruct patients what to do in the event pills are missed. See “What to Do if You Miss Capsules” section in FDA-approved patient labeling.
- Use a back-up or alternative method of contraception when enzyme inducers are used with TAYTULLA.
- COCs may reduce breast milk production. This is less likely to occur if breastfeeding is well established.
- Women who start COCs postpartum, and who have not yet had a period, should use an additional method of contraception until they have taken a pink capsule for 7 consecutive days.
- Amenorrhea may occur. Rule out pregnancy in the event of amenorrhea in two or more consecutive cycles.

Distributed by:
AbbVie Inc.
North Chicago, IL 60064

© 2024 AbbVie. All rights reserved.

Taytulla and its design are trademarks of Allergan Pharmaceuticals International Limited, an AbbVie company.

v3.3USPI5862

FDA-Approved Patient Labeling

Guide for Using TAYTULLA (Norethindrone Acetate and Ethinyl Estradiol Capsules and Ferrous Fumarate Capsules)

WARNING TO WOMEN WHO SMOKE

Do not use TAYTULLA if you smoke cigarettes and are over 35 years old. Smoking increases your risk of serious cardiovascular side effects (heart and blood vessel problems) from birth control pills, including death from heart attack, blood clots or stroke. This risk increases with age and the number of cigarettes you smoke.

Birth control pills help to lower the chances of becoming pregnant when taken as directed. They do not protect against HIV infection (AIDS) and other sexually transmitted infections.

What is TAYTULLA?

TAYTULLA is a birth control pill. It contains two female hormones, an estrogen called ethinyl estradiol, and a progestin called norethindrone acetate.

How well does TAYTULLA work?

Your chance of getting pregnant depends on how well you follow the directions for taking your birth control pills. The better you follow the directions, the less chance you have of getting pregnant.

Based on the results of one clinical study of a 24-day regimen of norethindrone acetate 1 mg/ethinyl estradiol 0.020 mg tablets lasting six months, about 1 to 4 out of 100 women may get pregnant during the first year they use TAYTULLA.

Women with a BMI above 35 kg/m^2 were not studied in the clinical trial, so it is not known how well TAYTULLA protects against pregnancy in such women. If you are overweight, discuss with your healthcare provider whether TAYTULLA is the best choice for you.

The following chart shows the chance of getting pregnant for women who use different methods of birth control. Each box on the chart contains a list of birth control methods that are similar in effectiveness. The most effective methods are at the top of the chart. The box on the bottom of the chart shows the chance of getting pregnant for women who do not use birth control and are trying to get pregnant.

How do I take TAYTULLA?

1. Be sure to read these directions before you start taking your capsules or anytime you are not sure what to do.

2. The right way to take the capsule is to take one capsule every day at the same time in the order directed on the package. TAYTULLA can be taken without regard to meals.

If you miss capsules you could get pregnant. This includes starting the pack late. The more capsules you miss, the more likely you are to get pregnant. See “WHAT TO DO IF YOU MISS CAPSULES” below.

3. Many women have spotting or light bleeding at unexpected times, or may feel sick to their stomach during the first 1 to 3 packs of capsules.

If you do have spotting or light bleeding or feel sick to your stomach, do not stop taking the capsules. The problem will usually go away. If it does not go away, check with your healthcare provider.

4. Missing capsules can also cause spotting or light bleeding, even when you make up these missed capsules.

On the days you take two capsules, to make up for missed capsules, you could also feel a little sick to your stomach.

5. If you have vomiting (within 3 to 4 hours after you take your capsule), you should follow the instructions for "WHAT TO DO IF YOU MISS CAPSULES." If you have diarrhea or if you take certain medicines, including some antibiotics and some herbal products such as St. John's Wort, your capsules may not work as well.

Use a back-up method (such as condoms and spermicides) until you check with your healthcare provider.

6. If you have trouble remembering to take TAYTULLA, talk to your healthcare provider about how to make capsule-taking easier or about using another method of birth control.

7. If you have any questions or are unsure about the information in this leaflet, call your healthcare provider.

Before You Start Taking Your TAYTULLA

1. Decide What Time of Day You Want to Take Your Capsule. It is important to take TAYTULLA in the order directed on the package at the same time every day. TAYTULLA can be taken without regard to meals.

2. Look at Your Capsule Pack – It has 28 Capsules

The TAYTULLA-pill pack has 24 "active" pink capsules (with hormones) to be taken for 24 days, followed by 4 "reminder" maroon capsules (without hormones) to be taken for the next four days.

3. Also look for:

a) Where on the pack to start taking capsules,

b) In what order to take the capsules (follow the arrows shown in the picture above)

c) The week numbers as shown in the picture above.

4. Be sure you have ready at all times

a) another kind of birth control (such as a condoms and spermicide) to use as a back-up in case you miss capsules, and

b) an extra, full pill pack.

When to Start the First Pack of Capsules

You have a choice for which day to start taking your first pack of capsules. Decide with your healthcare provider which is the best day for you. Pick a time of day which will be easy to remember.

Day 1 Start:

1. Pick the day label strip that starts with the first day of your period (this is the day you start bleeding or spotting, even if it is almost midnight when the bleeding begins).
2. Place this day label strip on the capsule dispenser over the area that has the days of the week (starting with Sunday) printed on the plastic.
3. Take the first pink pill of the pack during the first 24 hours of your period.
4. You will not need to use a back-up method of birth control, since you are starting the capsule at the beginning of your period. However, if you start TAYTULLA later than the first day of your period, you should use another method of birth control (such as a condom and spermicide) as a back-up method until you have taken 7 pink capsules.

Sunday Start:

1. Take the first pink capsule of the pack on the Sunday after your period starts, even if you are still bleeding. If your period begins on Sunday, start the pack that same day.
2. Use another method of birth control (such as a condom and spermicide) as a back-up method if you have sex anytime from the Sunday you start your first pack until the next Sunday (7 days). This also applies if you start TAYTULLA after having been pregnant, and you have not had a period since your pregnancy.

When You Switch From a Different Birth Control Tablet

When switching from another birth control pill, finish all the tablets, then TAYTULLA should be started on the same day that a new pack of the previous birth control tablet would have been started.

When You Switch From Another Type of Birth Control Method

When switching from a transdermal patch or vaginal ring, finish the 21 days of use, wait 7 days, then TAYTULLA should be started when the next application would have been due.

When switching from an injection, TAYTULLA should be started when the next injection would have been due. When switching from an intrauterine device or an implant, TAYTULLA should be started on the day of removal.

What to Do During the Month

1. Take one capsule at the same time every day until the pack is empty.

Do not skip capsules even if you are spotting or bleeding between monthly periods or feel sick to your stomach (nausea).

2. Do not skip capsules even if you do not have sex very often.

When you finish a pack of capsules, start the next pack on the day after your last maroon capsule. Do not wait any days between packs.

What to Do if You Miss Capsules

TAYTULLA may not be as effective if you miss any pink capsules, especially if you miss the first few or the last few pink capsules in a pack.

If you miss 1 pink capsule:

1. Take the capsule as soon as you remember. Take the next capsule at your regular time. This means you may take two capsules in one day.
2. You do not need to use a back-up birth control method if you have sex.

If you miss 2 pink capsules in a row in week 1 OR week 2 of your pack:

1. Take two capsules on the day you remember and two capsules the next day.
2. Then take one capsule a day until you finish the pack.
3. You could become pregnant if you have sex in the 7 days after you restart your capsules. You must use another birth control method (such as a condom and spermicide) as a back-up for those 7 days.

If you miss 2 pink capsules in a row in week 3 or week 4 of your pack:
1. If you are a Day 1 Starter:
Throw out the rest of the TAYTULLA pack and start a new pack that same day.

If you are a Sunday Starter:
Keep taking one capsule every day until Sunday. On Sunday, throw out the rest of the pack and start a new pack of capsules that same day.

2. You could become pregnant if you have sex in the 7 days after you restart your capsules. You must use another birth control method (such as a condom and spermicide) as a back-up for those 7 days.
3. You may not have your period this month but this is expected. However, if you miss your period two months in a row, call your healthcare provider because you might be pregnant.

If you miss 3 or more pink capsules in a row during any week:
1. If you are a Day 1 Starter:
Throw out the rest of the capsule pack and start a new pack that same day.

If you are a Sunday Starter:
Keep taking 1 capsule every day until Sunday. On Sunday, throw out the rest of the pack and start a new pack of capsules that same day.

2. You could become pregnant if you have sex on the days when you missed capsules or during the first 7 days after you restart your capsules. You must use another birth control method (such as a condom and spermicide) as a back-up the next time you have sex and for the first 7 days after you restart your capsules.
3. You may not have your period this month but this is expected. However, if you miss your period two months in a row, call your healthcare provider because you might be pregnant.

If you miss any of the 4 maroon capsules in Week 4:

1. Throw away the capsules you missed.
2. Keep taking one capsule each day until the pack is empty.
3. You do not need a back-up method.
4. Start the next pack of TAYTULLA as scheduled.

Finally, if you are still not sure what to do about the capsules you have missed:

1. Use a back-up method (such as a condom and spermicide) anytime you have sex.
2. Contact your healthcare provider and continue taking one active pink capsule each day until otherwise directed.

Who should not take TAYTULLA?

Your healthcare provider will not give you TAYTULLA if you have:

- Ever had blood clots in your arms, legs (deep vein thrombosis), lungs (pulmonary embolism), or eyes (retinal thrombosis)
- Ever had a stroke
- Ever had a heart attack
- Certain heart valve problems or heart rhythm abnormalities that can cause blood clots to form in the heart
- An inherited problem with your blood that makes it clot more than normal
- High blood pressure that medicine cannot control
- Diabetes with kidney, eye, nerve, or blood vessel damage
- Ever had certain kinds of severe migraine headaches with aura, numbness, weakness or changes in vision, or have any migraine headaches if you are over age 35
- Ever had breast cancer, which may be sensitive to female hormones
- Liver disease, including liver tumors
- Take any Hepatitis C drug combination containing ombitasvir/paritaprevir/ritonavir, with or without dasabuvir. This may increase levels of the liver enzyme “alanine aminotransferase” (ALT) in the blood.

Also, do not take birth control pills if you:

- Smoke and are over 35 years old
- Are or suspect you are pregnant
- Have any unexplained bleeding from the vagina

Birth control pills may not be a good choice for you if you have ever had jaundice (yellowing of the skin or eyes) caused by pregnancy, also called cholestasis of pregnancy.

Tell your healthcare provider if you have ever had any of the above conditions (your healthcare provider may recommend another method of birth control).

What else should I know about taking TAYTULLA?

Birth control pills do not protect you against any sexually transmitted infection, including HIV, the virus that causes AIDS.

Do not skip any pills, even if you do not have sex often.

If you miss a period, you could be pregnant. However, some women miss periods or have light periods on birth control pills, even when they are not pregnant. Contact your healthcare provider for advice if you:

- Think you are pregnant
- Miss one period and have not taken your birth control pills every day
- Miss two periods in a row

Birth control pills should not be taken during pregnancy. However, birth control pills taken by accident during pregnancy are not known to cause birth defects.

You should stop TAYTULLA at least four weeks before you have surgery and not restart it until at least two weeks after the surgery, due to an increased risk of blood clots.

If you are breastfeeding, consider another birth control method until you are ready to stop breastfeeding. Birth control pills that contain estrogen, like TAYTULLA, may decrease the amount of milk you make. A small amount of the pill's hormones pass into breast milk.

Tell your healthcare provider about all medicines and herbal products that you take. Some medicines and herbal products may make birth control pills less effective, including:

- barbiturates
- bosentan
- carbamazepine
- felbamate
- griseofulvin
- oxcarbazepine
- phenytoin
- rifampin
- St. John’s wort
- topiramate

Use a back-up or alternative birth control method when you take medicines that may make birth control pills less effective.

Birth control pills may interact with lamotrigine, an anticonvulsant used for epilepsy. This may increase the risk of seizures, so your healthcare provider may need to adjust the dose of lamotrigine.

If you have vomiting or diarrhea, your birth control pills may not work as well. Use another birth control method, like a condom and spermicide, until you check with your healthcare provider.

Women on thyroid hormone replacement therapy may need increased doses of thyroid hormone.

If you are scheduled for any laboratory tests, tell your healthcare provider that you are taking birth control pills. Certain blood tests may be affected by birth control pills.

What are the most serious risks of taking TAYTULLA?

Like pregnancy, birth control pills increase the risk of serious blood clots, especially in women who have other risk factors, such as smoking, obesity, or age greater than 35. This increased risk is highest when you first start taking birth control pills and when you restart the same or different birth control pills after not using them for a month or more.

It is possible to die from a problem caused by a blood clot, such as a heart attack or a stroke.

Some examples of serious blood clots are blood clots in the:

- Legs (deep vein thrombosis)
- Lungs (pulmonary embolus)
- Eyes (loss of eyesight)
- Heart (heart attack)
- Brain (stroke)

Women who take birth control pills may get:

- High blood pressure
- Gallbladder problems
- Rare cancerous or noncancerous liver tumors

All of these events are uncommon in healthy women.

Call your healthcare provider right away if you have:

- Persistent leg pain
- Sudden shortness of breath
- Sudden blindness, partial or complete
- Severe pain or pressure in your chest
- Sudden, severe headache unlike your usual headaches
- Weakness or numbness in an arm or leg, or trouble speaking
- Yellowing of the skin or eyeballs

What are the common side effects of birth control pills?

The most common side effects of birth control pills are:

- Spotting or bleeding between menstrual periods
- Nausea
- Breast tenderness
- Headache

These side effects are usually mild and usually disappear with time.

Less common side effects are:

- Acne
- Less sexual desire
- Bloating or fluid retention
- Blotchy darkening of the skin, especially on the face
- High blood sugar, especially in women who already have diabetes
- High fat (cholesterol, triglyceride) levels in the blood
- Depression, especially if you have had depression in the past. Call your healthcare provider immediately if you have any thoughts of harming yourself
- Problems tolerating contact lenses
- Weight gain

This is not a complete list of possible side effects. Talk to your healthcare provider if you develop any side effects that concern you. You may report side effects to the FDA at 1-800-FDA-1088.

No serious problems have been reported from a birth control pill overdose, even when accidentally taken by children.

Do birth control pills cause cancer?

It is not known if hormonal birth control pills cause breast cancer. Some studies, but not all, suggest that there could be a slight increase in the risk of breast cancer among current users with longer duration of use.

If you have breast cancer now, or have had it in the past, do not use hormonal birth control because some breast cancers are sensitive to hormones.

Women who use birth control pills may have a slightly higher chance of getting cervical cancer. However, this may be due to other reasons such as having more sexual partners.

What should I know about my period when taking TAYTULLA?

Irregular vaginal bleeding or spotting may occur while you are taking TAYTULLA. Irregular bleeding may vary from slight staining between menstrual periods to breakthrough bleeding, which is a flow much like a regular period. Irregular bleeding occurs most often during the first few months of oral contraceptive use, but may also occur after you have been taking the pill for some time. Such bleeding may be temporary and usually does not indicate any serious problems. It is important to continue taking your pills on schedule. If the bleeding occurs in more than one cycle, is unusually heavy, or lasts for more than a few days, call your healthcare provider.

Some women may not have a menstrual period but this should not be cause for alarm as long has you have taken the pills according to direction.

What if I miss my scheduled period when taking TAYTULLA?

It is not uncommon to miss your period. However, if you go two or more months in a row without a period, or you miss your period after a month where you did not take all your pills correctly, call your healthcare provider because you may be pregnant. Also notify your healthcare provider if you have symptoms of pregnancy such as morning sickness or unusual breast tenderness. Stop taking TAYTULLA if you are pregnant.

What if I want to become pregnant?

You may stop taking the capsule whenever you wish. Consider a visit with your healthcare provider for a pre-pregnancy checkup before you stop taking the capsule.

General Advice about TAYTULLA

Your healthcare provider prescribed TAYTULLA for you. Please do not share TAYTULLA with anyone else. Keep TAYTULLA out of the reach of children.

If you have concerns or questions, ask your healthcare provider. You may also ask your pharmacist for a more detailed label written for healthcare professionals.

This Patient Information has been approved by the U.S. Food and Drug Administration.

Revised: 10/2024

Distributed by:
AbbVie Inc.
North Chicago, IL 60064

©2024 AbbVie. All rights reserved.

Taytulla and its design are trademarks of Allergan Pharmaceuticals International Limited, an AbbVie company.

v3.2MG5862

PRINCIPAL DISPLAY PANEL

NDC 0023-5862-30
Rx only
28-DAY REGIMEN

Taytulla®
(norethindrone acetate and
ethinyl estradiol capsules and
ferrous fumarate capsules)
1 mg/20 mcg

Five PATIENT INSERTS are enclosed for your use when dispensing
Taytulla® (norethindrone acetate and ethinyl estradiol
capsules and ferrous fumarate capsules).

PROVIDES 24 DAYS
OF ACTIVE THERAPY.
abbvie